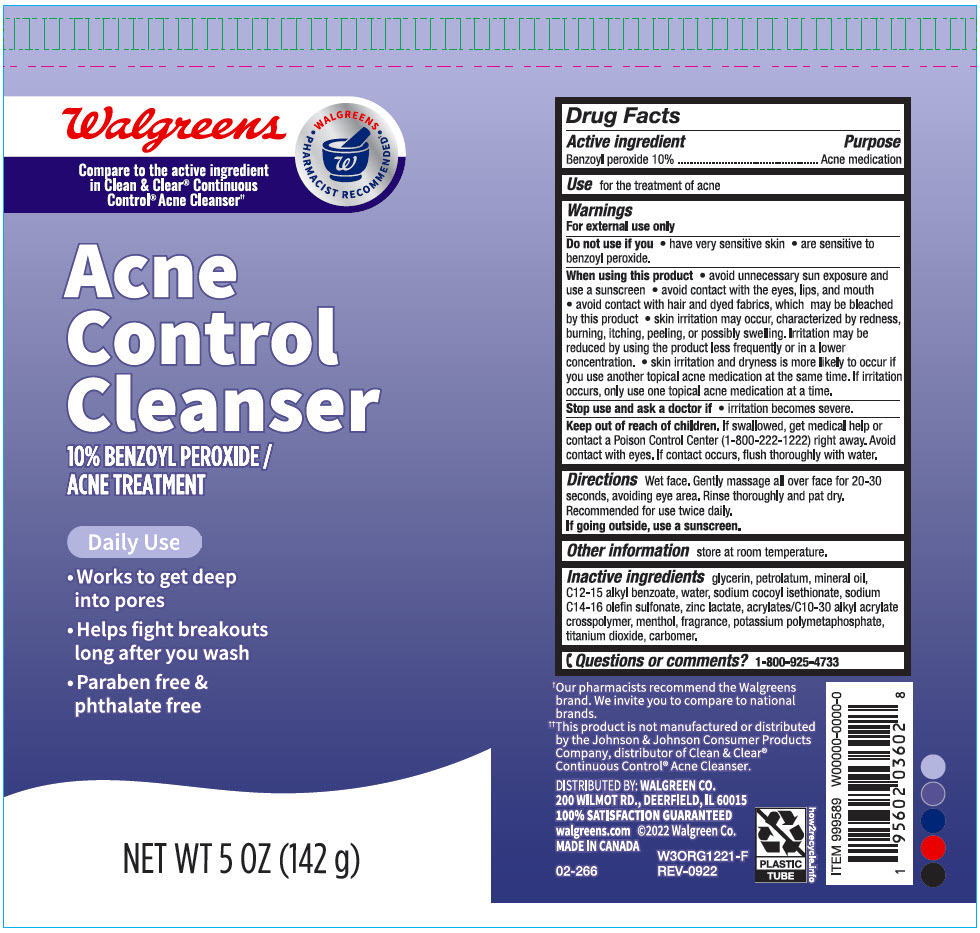 DRUG LABEL: Walgreens Acne Control Cleanser
NDC: 0363-3602 | Form: LOTION
Manufacturer: Walgreen Company
Category: otc | Type: HUMAN OTC DRUG LABEL
Date: 20241031

ACTIVE INGREDIENTS: Benzoyl Peroxide 100 mg/1 g
INACTIVE INGREDIENTS: Glycerin; Petrolatum; Mineral Oil; ALKYL (C12-15) BENZOATE; Water; Sodium Cocoyl Isethionate; Sodium C14-16 Olefin Sulfonate; Zinc Lactate; CARBOMER INTERPOLYMER TYPE A (ALLYL SUCROSE CROSSLINKED); MENTHOL, UNSPECIFIED FORM; POTASSIUM METAPHOSPHATE; Titanium Dioxide; CARBOMER HOMOPOLYMER, UNSPECIFIED TYPE

Walgreens Acne Control Cleanser
Acne Medication

Drug Facts

Active ingredient

Benzoyl peroxide 10%

Purpose

Acne Medication

Use

for the treatment of acne

Warnings

For external use only

Do not use if you

- have very sensitive skin
- are sensitive to benzoyl peroxide.

When using this product

- avoid unnecessary sun exposure and use a sunscreen
- avoid contact with the eyes, lips, and mouth
- avoid contact with hair and dyed fabrics, which may be bleached by this product
- skin irritation may occur, characterized by redness, burning, itching, peeling, or possibly swelling. Irritation may be reduced by using the product less frequently or in a lower concentration.
- skin irritation and dryness is more likely to occur if you use another topical acne medication at the same time. If irritation occurs, only use one topical acne medication at a time.

Stop use and consult a doctor if

- irritation becomes severe.

Keep out of reach of children. If swallowed, get medical help or contact a Poison Control Center (1-800-222-1222) right away. Avoid contact with eyes. If contact occurs, flush thoroughly with water.

Directions

Wet face. Gently massage all over face for 20-30 seconds, avoiding eye area. Rinse thoroughly and pat dry.

Recommended for use twice daily.

If going outside, use a sunscreen.

Other information

store at room temperature.

Inactive ingredients

glycerin, petrolatum, mineral oil, C12-15 alkyl benzoate, water, sodium cocoyl isethionate, sodium C14-16 olefin sulfonate, zinc lactate, acrylates/C10-30 alkyl acrylate crosspolymer, menthol, fragrance, potassium polymetaphosphate, titanium dioxide, carbomer.

Questions or comments?

1-800-925-4733

DISTRIBUTED BY: WALGREEN CO.
200 WILMOT RD., DEERFIELD, IL 60015

PRINCIPAL DISPLAY PANEL - 142 g Tube Label

Walgreens

Compare to the active ingredient
in Clean & Clear® Continuous
Control® Acne Cleanser††

• WALGREENS •
PHARMACIST RECOMMENDED†

Acne
Control
Cleanser

10% BENZOYL PEROXIDE /
ACNE TREATMENT

Daily Use

- Works to get deep
  into pores
- Helps fight breakouts
  long after you wash
- Paraben free &
  phthalate free

NET WT 5 OZ (142 g)